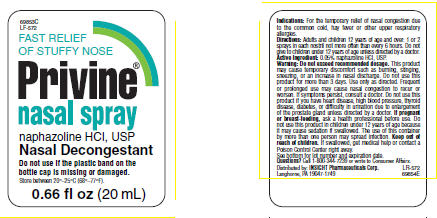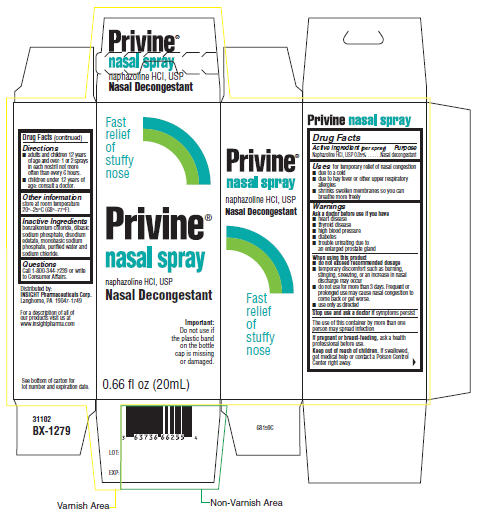 DRUG LABEL: Privine
NDC: 63736-662 | Form: SPRAY
Manufacturer: Insight Pharmaceuticals
Category: otc | Type: HUMAN OTC DRUG LABEL
Date: 20090731

ACTIVE INGREDIENTS: Naphazoline Hydrochloride 0.1 mL/20 mL
INACTIVE INGREDIENTS: benzalkonium chloride; sodium phosphate, dibasic; edetate disodium; sodium phosphate, monobasic; water; sodium chloride

Privine®
nasal spray

Drug Facts

Active ingredient (per spray)

Naphazoline HCl, USP 0.05%

Purpose

Nasal decongestant

Uses

for temporary relief of nasal congestion

- due to a cold
- due to hay fever or other upper respiratory allergies
- shrinks swollen membranes so you can breathe more freely

Warnings

Ask a doctor before use if you have

- heart disease
- thyroid disease
- high blood pressure
- diabetes
- trouble urinating due to an enlarged prostate gland

When using this product

- do not exceed recommended dosage
- temporary discomfort such as burning, stinging, sneezing, or an increase in nasal discharge may occur
- do not use for more than 3 days. Frequent or prolonged use may cause nasal congestion to come back or get worse.
- use only as directed

Stop use and ask a doctor if symptoms persist

The use of this container by more than one person may spread infection

PREGNANCY OR BREAST FEEDING

If pregnant or breast-feeding, ask a health professional before use.

Keep out of reach of children. If swallowed, get medical help or contact a Poison Control Center right away.

Directions

- adults and children 12 years of age and over: 1 or 2 sprays in each nostril not more often than every 6 hours.
- children under 12 years of age: consult a doctor.

Other information

store at room temperature 20°–25°C (68°–77°F).

Inactive Ingredients

benzalkonium chloride, dibasic sodium phosphate, disodium edetate, monobasic sodium phosphate, purified water and sodium chloride.

Questions

Call 1-800-344-7239 or write to Consumer Affairs.

Distributed by:
INSIGHT Pharmaceuticals Corp.
Langhorne, PA 19047-1749

PRINCIPAL DISPLAY PANEL - 20 mL spray label

69853C
LF-572

FAST RELIEF
OF STUFFY NOSE

Privine®
nasal spray
naphazoline HCl, USP
Nasal Decongestant

Do not use if the plastic band on the
bottle cap is missing or damaged.
Store between 20°–25°C (68°–77°F).

0.66 fl oz (20 mL)

PRINCIPAL DISPLAY PANEL - 20 mL spray carton

Fast
relief
of
stuffy
nose

Privine®
nasal spray
naphazoline HCl, USP
Nasal Decongestant

Important:
Do not use if
the plastic band
on the bottle
cap is missing
or damaged.

0.66 fl oz (20mL)